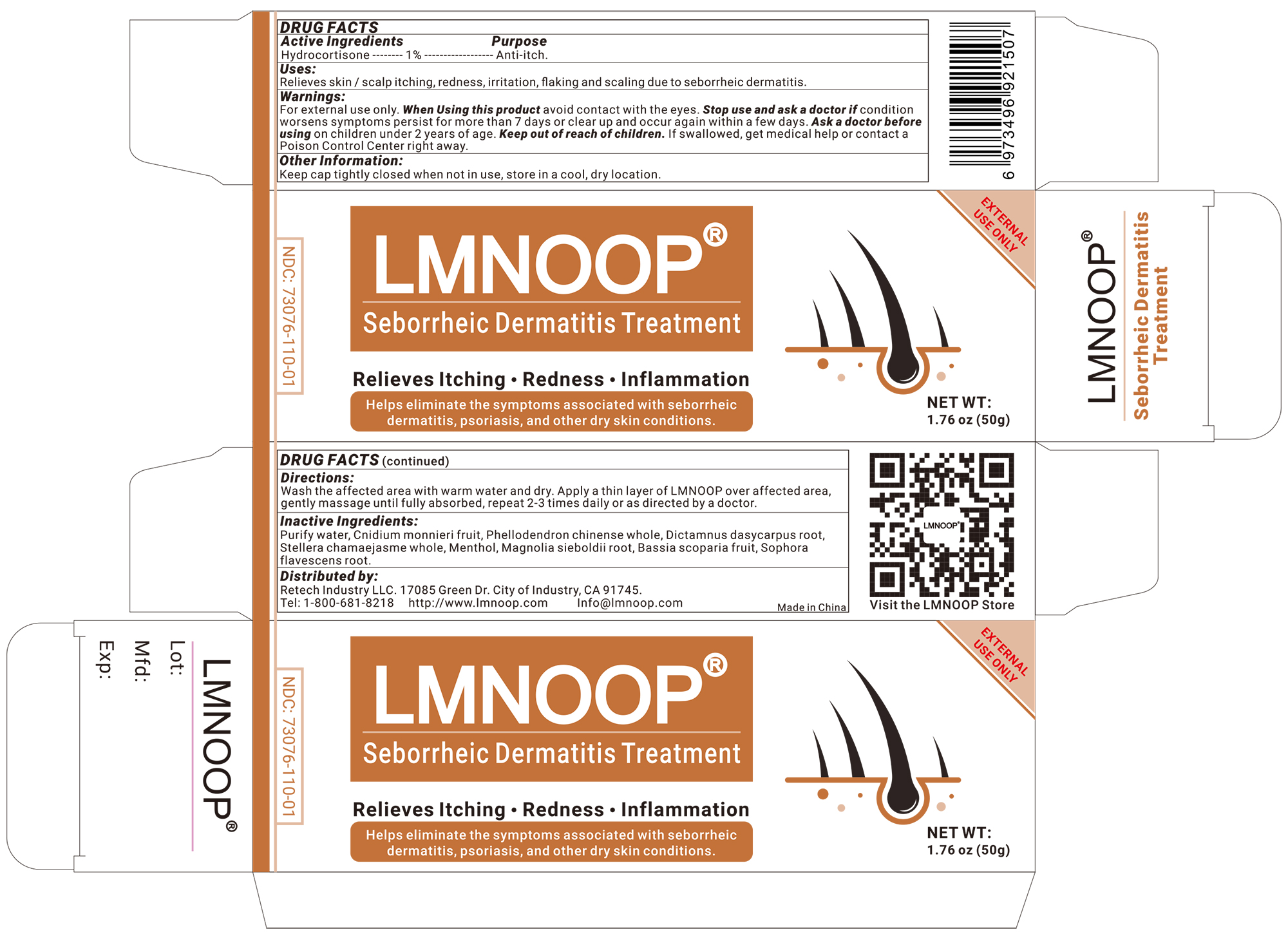 DRUG LABEL: LMNOOP Rosacea Cream
NDC: 73076-137 | Form: CREAM
Manufacturer: Shenzhen Ishan Technology Co., Ltd
Category: homeopathic | Type: HUMAN OTC DRUG LABEL
Date: 20260213

ACTIVE INGREDIENTS: OATMEAL 1 g/100 g
INACTIVE INGREDIENTS: CNIDIUM MONNIERI FRUIT 3 g/100 g; WATER; MENTHOL 1 g/100 g; MAGNOLIA SIEBOLDII ROOT 3 g/100 g; DICTAMNUS DASYCARPUS ROOT 3 g/100 g; SOPHORA FLAVESCENS ROOT 5 g/100 g; STELLERA CHAMAEJASME WHOLE 3 g/100 g; BASSIA SCOPARIA FRUIT 3 g/100 g

Active ingredients

Colloidal Oatmeal--1%--Skin protectant.

Inactive Ingredients

Purify water, dictamnus dasycarpus root, stellera chamaejasme whole, sophora flavescens root, cnidium monnieri fruit, phellodendron chinense whole, bassia scoparia fruit, Menthol.

Keep out of reach of children

if swallowed, call poison control or seek medical help.

Ask a doctor

before using on children under 2 years of age.

Stop use

if condition worsens, symptoms last more than 7 days or clear up and occur again within a few days, or there is no improvement of athlete's foot or psoriasis within 4 weeks or jock itch with 2 weeks.

Uses

Anti-bacterial, reduces itchy and painful skin conditions due to eczema, athletes foot, psoriasis, jock itch, rash, skin yeast infection and more.

Other information

Store at room temperature.

Directions

Wash and dry affected area, apply a thin layer of LMNOOP over affected area, gently massage until fully absorbed, repeat 2-3 times daily.

When using this product

o not get into eyes. do not apply to wounds or damaged skin.

Warnings

For external only